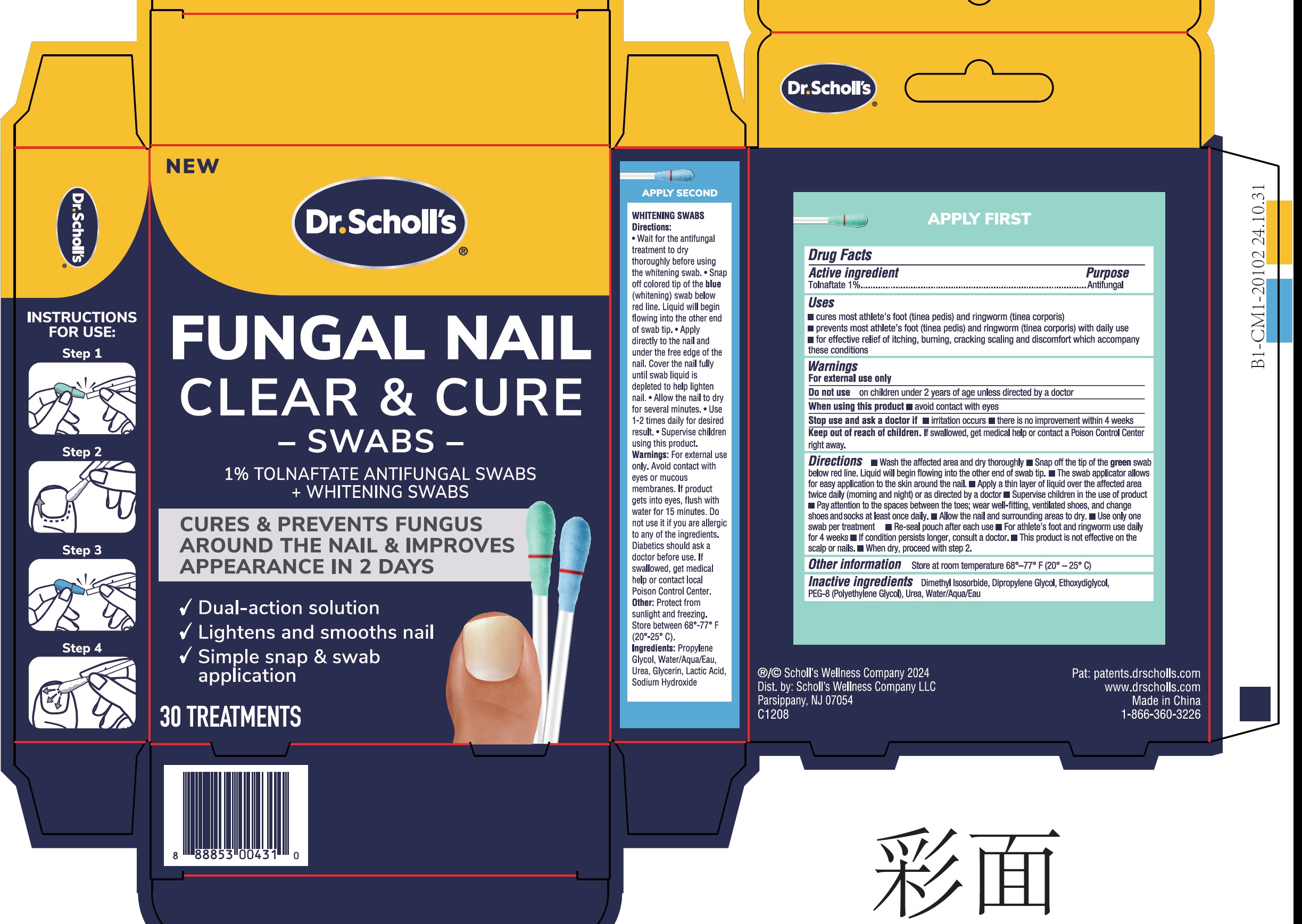 DRUG LABEL: Dr Scholls Fungal Nail Clear and Cure Tolnaftate Antifungal
NDC: 73469-0549 | Form: LIQUID
Manufacturer: Scholl's Wellness Company LLC
Category: otc | Type: HUMAN OTC DRUG LABEL
Date: 20260129

ACTIVE INGREDIENTS: TOLNAFTATE 11 mg/1 mL
INACTIVE INGREDIENTS: DIMETHYL ISOSORBIDE; DIPROPYLENE GLYCOL; DIETHYLENE GLYCOL MONOETHYL ETHER; POLYETHYLENE GLYCOL, UNSPECIFIED; UREA; WATER

Dr. Scholl's Fungal Nail Clear & Cure 1% Tolnaftate Antifungal Swabs

Active ingredient

Tolnaftate 1%

Purpose

Antifungal

Uses

- cures most athlete's foot (tinea pedis) and ringworm (tinea corporis)
- prevent most athlete's foot (tinea pedis) and ringworm (tinea corporis) with daily use
- for effective relief of itching, burning, cracking scaling and discomfort which accompany these conditions

Warnings

For external use only

Do not use

on children under 2 years of age unless directed by a doctor

When using this product

- avoid contact with eyes

Stop use and ask a doctor if

- irritation occurs
- there is no improvement within 4 weeks

Keep out of reach of children.

If swallowed, get medical help or contact a Poison Control Center right away.

Directions

- Wash the affected area and dry thoroughly
- Snap off the tip of the green swab below red line. Liquid will begin flowing into the other end of swab tip.
- The swab applicator allows for easy application to the skin around the nail.
- Apply a thin layer of liquid over the affected area twice daily (morning and night) or as directed by a doctor
- Supervise children in the use of product
- Pay attention to the spaces between the toes; wear well-fitting,ventilated shoes, and change shoes and socks at least once daily.
- Allow the nail and surrounding areas to dry.
- Use only one swab per treatment
- Re-seal pouch after each use
- For athlete's foot and ringworm use daily for 4 weeks
- If condition persists longer, consult a doctor.
- This product is not effective on the scalp or nails.
- When dry, proceed with step 2.

Other information

Store at room temperature 68º-77º F (20º - 25º C)

Inactive ingredients

Dimethyl Isosorbide, Dipropylene Glycol, Ethoxydiglycol, PEG-8 (Polyethylene Glycol), Urea, Water/Aqua/Eau